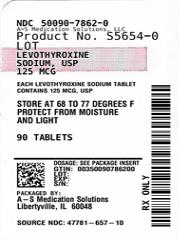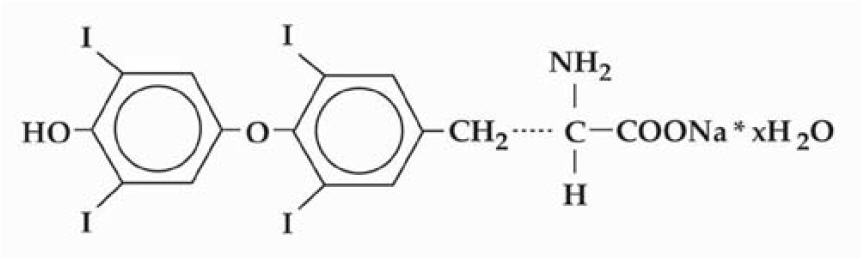 DRUG LABEL: levothyroxine sodium
NDC: 50090-7862 | Form: TABLET
Manufacturer: A-S Medication Solutions
Category: prescription | Type: HUMAN PRESCRIPTION DRUG LABEL
Date: 20260123

ACTIVE INGREDIENTS: LEVOTHYROXINE SODIUM 125 ug/1 1
INACTIVE INGREDIENTS: MICROCRYSTALLINE CELLULOSE; CALCIUM PHOSPHATE, DIBASIC, DIHYDRATE; POVIDONE, UNSPECIFIED; SODIUM STARCH GLYCOLATE TYPE A POTATO; MAGNESIUM STEARATE; BHT; YELLOW 6; RED 40; FD&C BLUE NO. 1

HIGHLIGHTS OF PRESCRIBING INFORMATION

These highlights do not include all the information needed to use LEVOTHYROXINE SODIUM TABLETS safely and effectively. See full prescribing information for LEVOTHYROXINE SODIUM TABLETS.
LEVOTHYROXINE SODIUM tablets, for oral use
Initial U.S. Approval: 2002

RECENT MAJOR CHANGES

Indications and Usage (1) | 11/2023
Dosage and Administration (2.2, 2.3) | 11/2023
Warnings and Precautions (5.1, 5.4) | 11/2023

WARNING: NOT FOR TREATMENT OF OBESITY OR FOR WEIGHT LOSS

See full prescribing information for complete boxed warning

- Thyroid hormones, including Levothyroxine Sodium Tablets should not be used for the treatment of obesity or for weight loss.
- Doses beyond the range of daily hormonal requirements may produce serious or even life threatening manifestations of toxicity (6, 10).

1 INDICATIONS AND USAGE

Levothyroxine Sodium Tablets are L-thyroxine (T4) indicated in adult and pediatric patients, including neonates, for:

- Hypothyroidism: As replacement therapy in primary (thyroidal), secondary (pituitary), and tertiary (hypothalamic) congenital or acquired hypothyroidism. (1)
- Pituitary Thyrotropin (Thyroid-Stimulating Hormone, TSH) Suppression: As an adjunct to surgery and radioiodine therapy in the management of thyrotropin-dependent well-differentiated thyroid cancer. (1)

Limitations of Use

- Not indicated for suppression of benign thyroid nodules and nontoxic diffuse goiter in iodine-sufficient patients
- Not indicated for treatment of hypothyroidism during the recovery phase of subacute thyroiditis

2 DOSAGE AND ADMINISTRATION

- Administer once daily, preferably on an empty stomach, one-half to one hour before breakfast. (2.1)
- Administer at least 4 hours before or after drugs that are known to interfere with absorption. (2.1)
- Evaluate the need for dose adjustments when regularly administering within one hour of certain foods that may affect absorption. (2.1)
- Starting dose depends on a variety of factors, including age, body weight, cardiovascular status, and concomitant medications. Peak therapeutic effect may not be attained for 4-6 weeks. (2.2)
- See full prescribing information for dosing in specific patient populations. (2.3)
- Adequacy of therapy determined with periodic monitoring of TSH and/or T4 as well as clinical status. (2.4)

3 DOSAGE FORMS AND STRENGTHS

Tablets: 25, 50, 75, 88, 100, 112, 125, 137, 150, 175, 200, and 300 mcg (3)

4 CONTRAINDICATIONS

- Uncorrected adrenal insufficiency (4)

5 WARNINGS AND PRECAUTIONS

- Serious risks related to overtreatment or undertreatment with Levothyroxine Sodium Tablets: Titrate the dose of Levothyroxine Sodium Tablets carefully and monitor response to titration. (5.1)
- Cardiac adverse reactions in the elderly and in patients with underlying cardiovascular disease: Initiate Levothyroxine Sodium Tablets at less than the full replacement dose because of the increased risk of cardiac adverse reactions, including atrial fibrillation. (2.3, 5.2, 8.5)
- Myxedema coma: Do not use oral thyroid hormone drug products to treat myxedema coma. (5.3)
- Acute adrenal crisis in patients with concomitant adrenal insufficiency: Treat with replacement glucocorticoids prior to initiation of Levothyroxine Sodium Tablets treatment. (5.4)
- Worsening of diabetic control: Therapy in patients with diabetes mellitus may worsen glycemic control and result in increased antidiabetic agent or insulin requirements. Carefully monitor glycemic control after starting, changing, or discontinuing thyroid hormone therapy. (5.5)
- Decreased bone mineral density associated with thyroid hormone over-replacement: Over-replacement can increase bone resorption and decrease bone mineral density. Give the lowest effective dose. (5.6)

6 ADVERSE REACTIONS

Adverse reactions associated with Levothyroxine Sodium Tablets therapy are primarily those of hyperthyroidism due to therapeutic overdosage: arrhythmias, myocardial infarction, dyspnea, muscle spasm, headache, nervousness, irritability, insomnia, tremors, muscle weakness, increased appetite, weight loss, diarrhea, heat intolerance, menstrual irregularities, and skin rash. (6)

To report SUSPECTED ADVERSE REACTIONS, contact Alvogen, Inc. at 1-866-770-3024 or FDA at 1-800-FDA-1088 or www.fda.gov/medwatch.

7 DRUG INTERACTIONS

See full prescribing information for drugs that affect thyroid hormone pharmacokinetics and metabolism (e.g., absorption, synthesis, secretion, catabolism, protein binding, and target tissue response) and may alter the therapeutic response to Levothyroxine Sodium Tablets. (7)

8 USE IN SPECIFIC POPULATIONS

Pregnancy may require the use of higher doses of Levothyroxine Sodium Tablets. (2.3, 8.1)

FULL PRESCRIBING INFORMATION

WARNING: NOT FOR TREATMENT OF OBESITY OR FOR WEIGHT LOSS

Thyroid hormones, including Levothyroxine Sodium Tablets, either alone or with other therapeutic agents, should not be used for the treatment of obesity or for weight loss.

In euthyroid patients, doses within the range of daily hormonal requirements are ineffective for weight reduction.

Larger doses may produce serious or even life threatening manifestations of toxicity, particularly when given in association with sympathomimetic amines such as those used for their anorectic effects [see Adverse Reactions (6), Drug Interactions (7.7), and Overdosage (10)].

1 INDICATIONS AND USAGE

Hypothyroidism

Levothyroxine Sodium Tablets are indicated in adult and pediatric patients, including neonates, as a replacement therapy in primary (thyroidal), secondary (pituitary), and tertiary (hypothalamic) congenital or acquired hypothyroidism.

Pituitary Thyrotropin (Thyroid-Stimulating Hormone, TSH) Suppression

Levothyroxine Sodium Tablets are indicated in adult and pediatric patients, including neonates, as an adjunct to surgery and radioiodine therapy in the management of thyrotropin-dependent well-differentiated thyroid cancer.

Limitations of Use

- Levothyroxine Sodium Tablets are not indicated for suppression of benign thyroid nodules and nontoxic diffuse goiter in iodine-sufficient patients as there are no clinical benefits and overtreatment with Levothyroxine Sodium Tablets may induce hyperthyroidism [see Warnings and Precautions (5.1)].
- Levothyroxine Sodium Tablets are not indicated for treatment of hypothyroidism during the recovery phase of subacute thyroiditis.

2 DOSAGE AND ADMINISTRATION

2.1 Important Administration Instructions

Administer Levothyroxine Sodium Tablets as a single daily dose, on an empty stomach, one-half to one hour before breakfast.

Administer Levothyroxine Sodium Tablets at least 4 hours before or after drugs known to interfere with Levothyroxine Sodium Tablets absorption [see Drug Interactions (7.1)].

Evaluate the need for dosage adjustments when regularly administering within one hour of certain foods that may affect Levothyroxine Sodium Tablets absorption [see Dosage and Administration (2.2 and 2.3), Drug Interactions (7.9) and Clinical Pharmacology (12.3)].

Administer Levothyroxine Sodium Tablets to pediatric patients who cannot swallow intact tablets by crushing the tablet, suspending the freshly crushed tablet in a small amount (5 to 10 mL) of water and immediately administering the suspension by spoon or dropper. Ensure the patient ingests the full amount of the suspension. Do not store the suspension. Do not administer in foods that decrease absorption of Levothyroxine Sodium Tablets, such as soybean-based infant formula [see Drug Interactions (7.9)].

2.2 Important Considerations for Dosing

The dosage of Levothyroxine Sodium Tablets for hypothyroidism or pituitary TSH suppression depends on a variety of factors including: the patient's age, body weight, cardiovascular status, concomitant medical conditions (including pregnancy), concomitant medications, co-administered food and the specific nature of the condition being treated [see Dosage and Administration (2.3), Warnings and Precautions (5), and Drug Interactions (7)]. Dosing must be individualized to account for these factors and dosage adjustments made based on periodic assessment of the patient's clinical response and laboratory parameters [see Dosage and Administration (2.4)].

For adult patients with primary hypothyroidism, titrate until the patient is clinically euthyroid and the serum TSH returns to normal [see Dosage and Administration (2.3)].

For secondary or tertiary hypothyroidism, serum TSH is not a reliable measure of Levothyroxine Sodium Tablets dosage adequacy and should not be used to monitor therapy. Use the serum free-T4 level to titrate Levothyroxine Sodium Tablets dosing until the patient is clinically euthyroid and the serum free-T4 level is restored to the upper half of the normal range [see Dosage and Administration (2.3)].

The peak therapeutic effect of a given dose of Levothyroxine Sodium Tablets may not be attained for 4 to 6 weeks.

2.3 Recommended Dosage and Titration

Primary, Secondary, and Tertiary Hypothyroidism in Adults

The recommended starting daily dosage of Levothyroxine Sodium Tablets in adults with primary, secondary, or tertiary hypothyroidism is based on age and comorbid cardiac conditions, as described in Table 1. For patients at risk of atrial fibrillation or patients with underlying cardiac disease, start with a lower dosage and titrate the dosage more slowly to avoid exacerbation of cardiac symptoms. Dosage titration is based on serum TSH or free-T4 [see Dosage and Administration (2.2)].

Table 1. Levothyroxine Sodium Tablets Dosing Guidelines for Hypothyroidism in Adults*
Patient Population | Starting Dosage | Dosage Titration Based on Serum TSH or Free-T4
Adults diagnosed with hypothyroidism | Full replacement dose is 1.6 mcg/kg/day. Some patients require a lower starting dose. | Titrate dosage by 12.5 to 25 mcg increments every 4 to 6 weeks, as needed until the patient is euthyroid.
Adults at risk for atrial fibrillation or with underlying cardiac disease | Lower starting dose (less than 1.6 mcg/kg/day) | Titrate dosage every 6 to 8 weeks, as needed until the patient is euthyroid.
Geriatric patients | Lower starting dose (less than 1.6 mcg/kg/day) | Titrate dosage every 6 to 8 weeks, as needed until the patient is euthyroid.
*Dosages greater than 200 mcg/day are seldom required. An inadequate response to daily dosages greater than 300 mcg/day is rare and may indicate poor compliance, malabsorption, drug interactions, or a combination of these factors [see Dosage and Administration (2.1) and Drug Interactions (7)].

Primary, Secondary, and Tertiary Hypothyroidism in Pediatric Patients

The recommended starting daily dosage of Levothyroxine Sodium Tablets in pediatric patients with primary, secondary, or tertiary hypothyroidism is based on body weight and changes with age as described in Table 2. Titrate the dosage (every 2 weeks) as needed based on serum TSH or free-T4 until the patient is euthyroid [see Dosage and Administration (2.2)].

Table 2. Levothyroxine Sodium Tablets Dosing Guidelines for Hypothyroidism in Pediatric Patients
Age | Starting Daily Dosage Per Kg Body Weight*
0-3 months | 10-15 mcg/kg/day
3-6 months | 8-10 mcg/kg/day
6-12 months | 6-8 mcg/kg/day
1-5 years | 5-6 mcg/kg/day
6-12 years | 4-5 mcg/kg/day
Greater than 12 years but growth and puberty incomplete | 2-3 mcg/kg/day
Growth and puberty complete | 1.6 mcg/kg/day
*Adjust dosage based on clinical response and laboratory parameters [see Dosage and Administration (2.4) and Use in Specific Populations (8.4)].

Pediatric Patients from Birth to 3 Months of Age at Risk for Cardiac Failure

Start at a lower starting dosage and increase the dosage every 4 to 6 weeks as needed based on clinical and laboratory response.

Pediatric Patients at Risk for Hyperactivity

To minimize the risk of hyperactivity, start at one-fourth the recommended full replacement dosage, and increase on a weekly basis by one-fourth the full recommended replacement dosage until the full recommended replacement dosage is reached.

Hypothyroidism in Pregnant Patients

For pregnant patients with pre-existing hypothyroidism, measure serum TSH and free-T4 as soon as pregnancy is confirmed and, at minimum, during each trimester of pregnancy. In pregnant patients with primary hypothyroidism, maintain serum TSH in the trimester-specific reference range. The recommended daily dosage of Levothyroxine Sodium Tablets in pregnant patients is described in Table 3.

Table 3. Levothyroxine Sodium Tablets Dosing Guidelines for Hypothyroidism in Pregnant Patients
Patient Population | Starting Dosage | Dose Adjustment and Titration
Pre-existing primary hypothyroidism with serum TSH above normal trimester-specific range | Pre-pregnancy dosage may increase during pregnancy | Increase Levothyroxine Sodium Tablets dosage by 12.5 to 25 mcg per day. Monitor TSH every 4 weeks until a stable dose is reached and serum TSH is within normal trimester-specific range. Reduce Levothyroxine Sodium Tablets dosage to pre-pregnancy levels immediately after delivery. Monitor serum TSH 4 to 8 weeks postpartum.
New onset hypothyroidism (TSH ≥ 10 mIU per liter) | 1.6 mcg/kg/day | Monitor serum TSH every 4 weeks and adjust Levothyroxine Sodium Tablets dosage until serum TSH is within normal trimester-specific range.
New onset hypothyroidism (TSH < 10 mIU per liter) | 1.0 mcg/kg/day | Monitor serum TSH every 4 weeks and adjust Levothyroxine Sodium Tablets dosage until serum TSH is within normal trimester-specific range.

TSH Suppression in Well-differentiated Thyroid Cancer in Adult and Pediatric Patients

The Levothyroxine Sodium Tablets dosage is based on the target level of TSH suppression for the stage and clinical status of thyroid cancer.

2.4 Monitoring TSH and/or Thyroxine (T4) Levels

Assess the adequacy of therapy by periodic assessment of laboratory tests and clinical evaluation. Persistent clinical and laboratory evidence of hypothyroidism despite an apparent adequate replacement dose of Levothyroxine Sodium Tablets may be evidence of inadequate absorption, poor compliance, drug interactions, or a combination of these factors.

Adults

In adult patients with primary hypothyroidism, monitor serum TSH levels after an interval of 6 to 8 weeks after any change in dosage. In patients on a stable and appropriate replacement dosage, evaluate clinical and biochemical response every 6 to 12 months and whenever there is a change in the patient’s clinical status.

Pediatric Patients

In patients with congenital hypothyroidism, assess the adequacy of replacement therapy by measuring both serum TSH and total or free-T4. Monitor TSH and total or free-T4 in pediatric patients as follows: 2 and 4 weeks after the initiation of treatment, 2 weeks after any change in dosage, and then every 3 to 12 months thereafter following dosage stabilization until growth is completed. Poor compliance or abnormal values may necessitate more frequent monitoring. Perform routine clinical examination, including assessment of development, mental and physical growth, and bone maturation, at regular intervals.

The general aim of therapy is to normalize the serum TSH level, TSH may not normalize in some patients due to in utero hypothyroidism causing a resetting of pituitary-thyroid feedback. Failure of the serum T4 to increase into the upper half of the normal range within 2 weeks of initiation of Levothyroxine Sodium Tablets therapy and/or of the serum TSH to decrease below 20 units per liter within 4 weeks may indicate the patient is not receiving adequate therapy. Assess compliance, dose of medication administered, and method of administration prior to increasing the dose of Levothyroxine Sodium Tablets [see Warnings and Precautions (5.1) and Use in Specific Populations (8.4)].

Secondary and Tertiary Hypothyroidism

Monitor serum free-T4 levels and maintain in the upper half of the normal range in these patients.

3 DOSAGE FORMS AND STRENGTHS

Levothyroxine Sodium Tablets, in the shape of caplet, are available as follows (Table 4):

Table 4. Levothyroxine Sodium Tablets Tablet Strengths and Identifying Features
Tablet Strength | Tablet Color | Tablet Markings
25 mcg | Orange | "T|4" and "25"
50 mcg | White | "T|4" and "50"
75 mcg | Violet | "T|4" and "75"
88 mcg | Mint Green | "T|4" and "88"
100 mcg | Yellow | "T|4" and "100"
112 mcg | Rose | "T|4" and "112"
125 mcg | Brown | "T|4" and "125"
137 mcg | Deep Blue | "T|4" and "137"
150 mcg | Light Blue | "T|4" and "150"
175 mcg | Lilac | "T|4" and "175"
200 mcg | Pink | "T|4" and "200"
300 mcg | Green | "T|4" and "300"

4 CONTRAINDICATIONS

Levothyroxine Sodium Tablets are contraindicated in patients with uncorrected adrenal insufficiency [see Warnings and Precautions (5.4)].

5 WARNINGS AND PRECAUTIONS

5.1 Serious Risks Related to Overtreatment or Undertreatment with Levothyroxine Sodium Tablets

Levothyroxine Sodium Tablets have a narrow therapeutic index. Overtreatment or undertreatment with Levothyroxine Sodium Tablets may have negative effects on growth and development, cardiovascular function, bone metabolism, reproductive function, cognitive function, gastrointestinal function, and glucose and lipid metabolism in adult or pediatric patients.

In pediatric patients with congenital and acquired hypothyroidism, undertreatment may adversely affect cognitive development and linear growth, and overtreatment is associated with craniosynostosis and acceleration of bone age [see Use in Specific Populations (8.4)].

Titrate the dose of Levothyroxine Sodium Tablets carefully and monitor response to titration to avoid these effects [see Dosage and Administration (2.4)]. Consider the potential for food or drug interactions and adjust the administration or dosage of Levothyroxine Sodium Tablets as needed [see Dosage and Administration (2.1), Drug Interactions (7.1, 7.9), and Clinical Pharmacology (12.3)].

5.2 Cardiac Adverse Reactions in the Elderly and in Patients with Underlying Cardiovascular Disease

Overtreatment with levothyroxine may cause an increase in heart rate, cardiac wall thickness, and cardiac contractility and may precipitate angina or arrhythmias, particularly in patients with cardiovascular disease and in elderly patients. Initiate Levothyroxine Sodium Tablets therapy in this population at lower doses than those recommended in younger individuals or in patients without cardiac disease [see Dosage and Administration (2.3) and Use in Specific Populations (8.5)].

Monitor for cardiac arrhythmias during surgical procedures in patients with coronary artery disease receiving suppressive Levothyroxine Sodium Tablets therapy. Monitor patients receiving concomitant Levothyroxine Sodium Tablets and sympathomimetic agents for signs and symptoms of coronary insufficiency.

If cardiac symptoms develop or worsen, reduce the Levothyroxine Sodium Tablets dose or withhold for one week and restart at a lower dose.

5.3 Myxedema Coma

Myxedema coma is a life-threatening emergency characterized by poor circulation and hypometabolism, and may result in unpredictable absorption of levothyroxine sodium from the gastrointestinal tract. Use of oral thyroid hormone drug products is not recommended to treat myxedema coma. Administer thyroid hormone products formulated for intravenous administration to treat myxedema coma.

5.4 Acute Adrenal Crisis in Patients with Concomitant Adrenal Insufficiency

Thyroid hormone increases metabolic clearance of glucocorticoids. Initiation of thyroid hormone therapy prior to initiating glucocorticoid therapy may precipitate an acute adrenal crisis in patients with adrenal insufficiency. Treat patients with adrenal insufficiency with replacement glucocorticoids prior to initiating treatment with Levothyroxine Sodium Tablets [see Contraindications (4)].

5.5 Worsening of Diabetic Control

Addition of levothyroxine therapy in patients with diabetes mellitus may worsen glycemic control and result in increased antidiabetic agent or insulin requirements. Carefully monitor glycemic control after starting, changing, or discontinuing Levothyroxine Sodium Tablets [see Drug Interactions (7.2)].

5.6 Decreased Bone Mineral Density Associated with Thyroid Hormone Over-Replacement

Increased bone resorption and decreased bone mineral density may occur as a result of levothyroxine over-replacement, particularly in post-menopausal women. The increased bone resorption may be associated with increased serum levels and urinary excretion of calcium and phosphorous, elevations in bone alkaline phosphatase, and suppressed serum parathyroid hormone levels. Administer the minimum dose of Levothyroxine Sodium Tablets that achieves the desired clinical and biochemical response to mitigate this risk.

6 ADVERSE REACTIONS

Adverse reactions associated with Levothyroxine Sodium Tablets therapy are primarily those of hyperthyroidism due to therapeutic overdosage [see Warnings and Precautions (5) and Overdosage (10)]. They include the following:

- General: fatigue, increased appetite, weight loss, heat intolerance, fever, excessive sweating
- Central nervous system: headache, hyperactivity, nervousness, anxiety, irritability, emotional lability, insomnia
- Musculoskeletal: tremors, muscle weakness, muscle spasm
- Cardiovascular: palpitations, tachycardia, arrhythmias, increased pulse and blood pressure, heart failure, angina, myocardial infarction, cardiac arrest
- Respiratory: dyspnea
- Gastrointestinal: diarrhea, vomiting, abdominal cramps, elevations in liver function tests
- Dermatologic: hair loss, flushing, rash
- Endocrine: decreased bone mineral density
- Reproductive: menstrual irregularities, impaired fertility

Seizures have been reported rarely with the institution of levothyroxine therapy.

Adverse Reactions in Pediatric Patients

Pseudotumor cerebri and slipped capital femoral epiphysis have been reported in pediatric patients receiving levothyroxine therapy. Overtreatment may result in craniosynostosis in infants who have not undergone complete closure of the fontanelles, and in premature closure of the epiphyses in pediatric patients still experiencing growth with resultant compromised adult height.

Hypersensitivity Reactions

Hypersensitivity reactions to inactive ingredients have occurred in patients treated with thyroid hormone products. These include urticaria, pruritus, skin rash, flushing, angioedema, various gastrointestinal symptoms (abdominal pain, nausea, vomiting and diarrhea), fever, arthralgia, serum sickness, and wheezing. Hypersensitivity to levothyroxine itself is not known to occur.

7 DRUG INTERACTIONS

7.1 Drugs Known to Affect Thyroid Hormone Pharmacokinetics

Many drugs can exert effects on thyroid hormone pharmacokinetics and metabolism (e.g., absorption, synthesis, secretion, catabolism, protein binding, and target tissue response) and may alter the therapeutic response to Levothyroxine Sodium Tablets (Tables 5 to 8).

Table 5. Drugs That May Decrease T4 Absorption (Hypothyroidism)
Potential impact: Concurrent use may reduce the efficacy of Levothyroxine Sodium Tablets by binding and delaying or preventing absorption, potentially resulting in hypothyroidism.
Drug or Drug Class | Effect
Phosphate Binders (e.g., calcium carbonate, ferrous sulfate, sevelamer, lanthanum) | Phosphate binders may bind to levothyroxine. Administer Levothyroxine Sodium Tablets at least 4 hours apart from these agents.
Orlistat | Monitor patients treated concomitantly with orlistat and Levothyroxine Sodium Tablets for changes in thyroid function.
Bile Acid Sequestrants (e.g., colesevelam, cholestyramine, colestipol) Ion Exchange Resins (e.g., Kayexalate) | Bile acid sequestrants and ion exchange resins are known to decrease levothyroxine absorption. Administer Levothyroxine Sodium Tablets at least 4 hours prior to these drugs or monitor TSH levels.
Proton Pump Inhibitors Sucralfate Antacids (e.g., aluminum & magnesium hydroxides, simethicone) | Gastric acidity is an essential requirement for adequate absorption of levothyroxine. Sucralfate, antacids and proton pump inhibitors may cause hypochlorhydria, affect intragastric pH, and reduce levothyroxine absorption. Monitor patients appropriately.

Table 6. Drugs That May Alter T4 and Triiodothyronine (T3) Serum Transport Without Affecting Free Thyroxine (FT4) Concentration (Euthyroidism)
Drug or Drug Class | Effect
Clofibrate Estrogen-containing oral contraceptives Estrogens (oral) Heroin / Methadone 5-Fluorouracil Mitotane Tamoxifen | These drugs may increase serum thyroxine-binding globulin (TBG) concentration.
Androgens / Anabolic Steroids Asparaginase Glucocorticoids Slow-Release Nicotinic Acid | These drugs may decrease serum TBG concentration.
Potential impact (below): Administration of these agents with Levothyroxine Sodium Tablets results in an initial transient increase in FT4. Continued administration results in a decrease in serum T4 and normal FT4 and TSH concentrations.
Salicylates (greater than 2 g/day) | Salicylates inhibit binding of T4 and T3 to TBG and transthyretin. An initial increase in serum FT4 is followed by return of FT4 to normal levels with sustained therapeutic serum salicylate concentrations, although total T4 levels may decrease by as much as 30%.
Other drugs: Carbamazepine Furosemide (greater than 80 mg IV) Heparin Hydantoins Non-Steroidal Anti-inflammatory Drugs - Fenamates | These drugs may cause protein-binding site displacement. Furosemide has been shown to inhibit the protein binding of T4 to TBG and albumin, causing an increase free T4 fraction in serum. Furosemide competes for T4-binding sites on TBG, prealbumin, and albumin, so that a single high dose can acutely lower the total T4 level. Phenytoin and carbamazepine reduce serum protein binding of levothyroxine, and total and free T4 may be reduced by 20% to 40%, but most patients have normal serum TSH levels and are clinically euthyroid. Closely monitor thyroid hormone parameters.

Table 7. Drugs That May Alter Hepatic Metabolism of T4 (Hypothyroidism)
Potential impact: Stimulation of hepatic microsomal drug-metabolizing enzyme activity may cause increased hepatic degradation of levothyroxine, resulting in increased Levothyroxine Sodium Tablets requirements.
Drug or Drug Class | Effect
Phenobarbital Rifampin | Phenobarbital has been shown to reduce the response to thyroxine. Phenobarbital increases L-thyroxine metabolism by inducing uridine 5'-diphospho-glucuronosyltransferase (UGT) and leads to a lower T4 serum levels. Changes in thyroid status may occur if barbiturates are added or withdrawn from patients being treated for hypothyroidism. Rifampin has been shown to accelerate the metabolism of levothyroxine.

Table 8. Drugs That May Decrease Conversion of T4 to T3
Potential impact: Administration of these enzyme inhibitors decreases the peripheral conversion of T4 to T3, leading to decreased T3 levels. However, serum T4 levels are usually normal but may occasionally be slightly increased.
Drug or Drug Class | Effect
Beta-adrenergic antagonists (e.g., Propranolol greater than 160 mg/day) | In patients treated with large doses of propranolol (greater than 160 mg/day), T3 and T4 levels change, TSH levels remain normal, and patients are clinically euthyroid. Actions of particular beta-adrenergic antagonists may be impaired when a hypothyroid patient is converted to the euthyroid state.
Glucocorticoids (e.g., Dexamethasone greater than or equal to 4 mg/day) | Short-term administration of large doses of glucocorticoids may decrease serum T3 concentrations by 30% with minimal change in serum T4 levels. However, long-term glucocorticoid therapy may result in slightly decreased T3 and T4 levels due to decreased TBG production (See above).
Other drugs: Amiodarone | Amiodarone inhibits peripheral conversion of levothyroxine (T4) to triiodothyronine (T3) and may cause isolated biochemical changes (increase in serum free-T4, and decreased or normal free-T3) in clinically euthyroid patients.

7.2 Antidiabetic Therapy

Addition of Levothyroxine Sodium Tablets therapy in patients with diabetes mellitus may worsen glycemic control and result in increased antidiabetic agent or insulin requirements. Carefully monitor glycemic control, especially when thyroid therapy is started, changed, or discontinued [see Warnings and Precautions (5.5)].

7.3 Oral Anticoagulants

Levothyroxine Sodium Tablets increase the response to oral anticoagulant therapy. Therefore, a decrease in the dose of anticoagulant may be warranted with correction of the hypothyroid state or when the Levothyroxine Sodium Tablets dose is increased. Closely monitor coagulation tests to permit appropriate and timely dosage adjustments.

7.4 Digitalis Glycosides

Levothyroxine Sodium Tablets may reduce the therapeutic effects of digitalis glycosides. Serum digitalis glycoside levels may decrease when a hypothyroid patient becomes euthyroid, necessitating an increase in the dose of digitalis glycosides.

7.5 Antidepressant Therapy

Concurrent use of tricyclic (e.g., amitriptyline) or tetracyclic (e.g., maprotiline) antidepressants and Levothyroxine Sodium Tablets may increase the therapeutic and toxic effects of both drugs, possibly due to increased receptor sensitivity to catecholamines. Toxic effects may include increased risk of cardiac arrhythmias and central nervous system stimulation. Levothyroxine Sodium Tablets may accelerate the onset of action of tricyclics. Administration of sertraline in patients stabilized on Levothyroxine Sodium Tablets may result in increased Levothyroxine Sodium Tablets requirements.

7.6 Ketamine

Concurrent use of ketamine and Levothyroxine Sodium Tablets may produce marked hypertension and tachycardia. Closely monitor blood pressure and heart rate in these patients.

7.7 Sympathomimetics

Concurrent use of sympathomimetics and Levothyroxine Sodium Tablets may increase the effects of sympathomimetics or thyroid hormone. Thyroid hormones may increase the risk of coronary insufficiency when sympathomimetic agents are administered to patients with coronary artery disease.

7.8 Tyrosine-Kinase Inhibitors

Concurrent use of tyrosine-kinase inhibitors such as imatinib may cause hypothyroidism. Closely monitor TSH levels in such patients.

7.9 Drug-Food Interactions

Consumption of certain foods may affect Levothyroxine Sodium Tablets absorption thereby necessitating adjustments in dosing [see Dosage and Administration (2.1)]. Soybean flour, cottonseed meal, walnuts, and dietary fiber may bind and decrease the absorption of Levothyroxine Sodium Tablets from the gastrointestinal tract. Grapefruit juice may delay the absorption of levothyroxine and reduce its bioavailability.

7.10 Drug-Laboratory Test Interactions

Consider changes in TBG concentration when interpreting T4 and T3 values. Measure and evaluate unbound (free) hormone and/or determine the free-T4 index (FT4I) in this circumstance. Pregnancy, infectious hepatitis, estrogens, estrogen-containing oral contraceptives, and acute intermittent porphyria increase TBG concentration. Nephrosis, severe hypoproteinemia, severe liver disease, acromegaly, androgens, and corticosteroids decrease TBG concentration. Familial hyper- or hypo-thyroxine binding globulinemias have been described, with the incidence of TBG deficiency approximating 1 in 9000.

8 USE IN SPECIFIC POPULATIONS

8.1 Pregnancy

Risk Summary

The clinical experience, including data from postmarketing studies, in pregnant women treated with oral levothyroxine to maintain euthyroid state have not reported increased rates of major birth defects, miscarriages, or other adverse maternal or fetal outcomes. There are risks to the mother and fetus associated with untreated hypothyroidism in pregnancy. Since TSH levels may increase during pregnancy, TSH should be monitored and Levothyroxine Sodium Tablets dosage adjusted during pregnancy (see Clinical Considerations). Animal reproductive studies have not been conducted with levothyroxine sodium. Levothyroxine Sodium Tablets should not be discontinued during pregnancy and hypothyroidism diagnosed during pregnancy should be promptly treated.

The estimated background risk of major birth defects and miscarriage for the indicated population is unknown. All pregnancies have a background risk of birth defect, loss, or other adverse outcomes. In the U.S. general population, the estimated background risk of major birth defects and miscarriage in clinically recognized pregnancies is 2% to 4% and 15% to 20%, respectively.

Clinical Considerations

Disease-Associated Maternal and/or Embryo/Fetal Risk

Maternal hypothyroidism during pregnancy is associated with a higher rate of complications, including spontaneous abortion, gestational hypertension, pre-eclampsia, stillbirth, and premature delivery. Untreated maternal hypothyroidism may have an adverse effect on fetal neurocognitive development.

Dose Adjustments During Pregnancy and the Postpartum Period

Pregnancy may increase Levothyroxine Sodium Tablets requirements. Serum TSH levels should be monitored and the Levothyroxine Sodium Tablets dosage adjusted during pregnancy. Since postpartum TSH levels are similar to preconception values, the Levothyroxine Sodium Tablets dosage should return to the pre-pregnancy dose immediately after delivery [see Dosage and Administration (2.3)].

8.2 Lactation

Risk Summary

Published studies report that levothyroxine is present in human milk following administration of oral levothyroxine. No adverse effects on the breastfed infant have been reported and there is no information on the effects of levothyroxine on milk production. Adequate levothyroxine treatment during lactation may normalize milk production in hypothyroid lactating mothers with low milk supply. The developmental and health benefits of breastfeeding should be considered along with the mother’s clinical need for Levothyroxine Sodium Tablets and any potential adverse effects on the breastfed infant from Levothyroxine Sodium Tablets or from the underlying maternal condition.

8.4 Pediatric Use

Levothyroxine Sodium Tablets are indicated in patients from birth to less than 17 years of age:

- As a replacement therapy in primary (thyroidal), secondary (pituitary), and tertiary (hypothalamic) congenital or acquired hypothyroidism.
- As an adjunct to surgery and radioiodine therapy in the management of thyrotropin-dependent well-differentiated thyroid cancer.

Rapid restoration of normal serum T4 concentrations is essential for preventing the adverse effects of congenital hypothyroidism on cognitive development as well as on overall physical growth and maturation. Therefore, initiate Levothyroxine Sodium Tablets therapy immediately upon diagnosis. Levothyroxine is generally continued for life in these patients [see Warnings and Precautions (5.1)].

Closely monitor infants during the first 2 weeks of Levothyroxine Sodium Tablets therapy for cardiac overload and arrhythmias.

8.5 Geriatric Use

Because of the increased prevalence of cardiovascular disease among the elderly, initiate Levothyroxine Sodium Tablets at less than the full replacement dose [see Dosage and Administration (2.3) and Warnings and Precautions (5.2)]. Atrial arrhythmias can occur in elderly patients. Atrial fibrillation is the most common of the arrhythmias observed with levothyroxine overtreatment in the elderly.

10 OVERDOSAGE

The signs and symptoms of overdosage are those of hyperthyroidism [see Warnings and Precautions (5) and Adverse Reactions (6)]. In addition, confusion and disorientation may occur.

Cerebral embolism, shock, coma, and death have been reported. Seizures occurred in a 3-year-old child ingesting 3.6 mg of levothyroxine. Symptoms may not necessarily be evident or may not appear until several days after ingestion of levothyroxine sodium.

Reduce the Levothyroxine Sodium Tablets dose or discontinue temporarily if signs or symptoms of overdosage occur. Initiate appropriate supportive treatment as dictated by the patient's medical status.

For current information on the management of poisoning or overdosage, contact the National Poison Control Center at 1-800-222-1222 or www.poison.org.

11 DESCRIPTION

Levothyroxine Sodium Tablets are L-thyroxine (T4) and contain the active ingredient, levothyroxine, a synthetic crystalline L-3,3',5,5'-tetraiodothyronine sodium salt. Synthetic T4 is chemically identical to that produced in the human thyroid gland. Levothyroxine (T4) sodium has an empirical formula of C15H10I4NNaO4•H2O, molecular weight of 798.86 g/mol (anhydrous), and structural formula as shown:

Levothyroxine Sodium Tablets are for oral administration and are available in the following strengths: 25 mcg, 50 mcg, 75 mcg, 88 mcg, 100 mcg, 112 mcg, 125 mcg, 137 mcg, 150 mcg, 175 mcg, 200 mcg, and 300 mcg. Each levothyroxine sodium tablet contains the inactive ingredients butylated hydroxytoluene, calcium phosphate dibasic dihydrate, magnesium stearate, microcrystalline cellulose, povidone, sodium starch glycolate, and color additive(s). Table 9 provides a listing of the color additives by tablet strength:

Table 9. Levothyroxine Sodium Tablets Color Additives
Strength (mcg) | Color additive(s)
25 | FD&C Yellow No. 6 Aluminum Lake [Note – FD&C Yellow No. 6 is orange in color.]
50 | None
75 | FD&C Red No. 40 Aluminum Lake, FD&C Blue No. 2 Aluminum Lake
88 | FD&C Blue No. 1 Aluminum Lake, FD&C Yellow No. 6 Aluminum Lake*, D&C Yellow No. 10 Aluminum Lake
100 | D&C Yellow No. 10 Aluminum Lake, FD&C Yellow No. 6 Aluminum Lake*
112 | D&C Red No. 27 & 30 Aluminum Lake
125 | FD&C Yellow No. 6 Aluminum Lake*, FD&C Red No. 40 Aluminum Lake, FD&C Blue No. 1 Aluminum Lake
137 | FD&C Blue No. 1 Aluminum Lake
150 | FD&C Blue No. 2 Aluminum Lake
175 | FD&C Blue No. 1 Aluminum Lake, D&C Red No. 27 & 30 Aluminum Lake
200 | FD&C Red No. 40 Aluminum Lake
300 | D&C Yellow No. 10 Aluminum Lake, FD&C Yellow No. 6 Aluminum Lake*, FD&C Blue No. 1 Aluminum Lake

12 CLINICAL PHARMACOLOGY

12.1 Mechanism of Action

Thyroid hormones exert their physiologic actions through control of DNA transcription and protein synthesis. Triiodothyronine (T3) and L-thyroxine (T4) diffuse into the cell nucleus and bind to thyroid receptor proteins attached to DNA. This hormone nuclear receptor complex activates gene transcription and synthesis of messenger RNA and cytoplasmic proteins.

The physiological actions of thyroid hormones are produced predominantly by T3, the majority of which (approximately 80%) is derived from T4 by deiodination in peripheral tissues.

12.2 Pharmacodynamics

Oral levothyroxine sodium is a synthetic T4 hormone that exerts the same physiologic effect as endogenous T4, thereby maintaining normal T4 levels when a deficiency is present.

12.3 Pharmacokinetics

Absorption

Absorption of orally administered T4 from the gastrointestinal tract ranges from 40% to 80%. The majority of the Levothyroxine Sodium Tablets dose is absorbed from the jejunum and upper ileum. The relative bioavailability of Levothyroxine Sodium Tablets, compared to an equal nominal dose of oral levothyroxine sodium solution, is approximately 94%. T4 absorption is increased by fasting, and decreased in malabsorption syndromes and by certain foods such as soybeans. Dietary fiber decreases bioavailability of T4. Absorption may also decrease with age. In addition, many drugs and foods affect T4 absorption [see Drug Interactions (7)].

Distribution

Circulating thyroid hormones are greater than 99% bound to plasma proteins, including thyroxine-binding globulin (TBG), thyroxine-binding prealbumin (TBPA), and albumin (TBA), whose capacities and affinities vary for each hormone. The higher affinity of both TBG and TBPA for T4 partially explains the higher serum levels, slower metabolic clearance, and longer half-life of T4 compared to T3. Protein-bound thyroid hormones exist in reverse equilibrium with small amounts of free hormone. Only unbound hormone is metabolically active. Many drugs and physiologic conditions affect the binding of thyroid hormones to serum proteins [see Drug Interactions (7)]. Thyroid hormones do not readily cross the placental barrier [see Use in Specific Populations (8.1)].

Elimination

Metabolism

T4 is slowly eliminated (Table 10). The major pathway of thyroid hormone metabolism is through sequential deiodination. Approximately 80% of circulating T3 is derived from peripheral T4 by monodeiodination. The liver is the major site of degradation for both T4 and T3, with T4 deiodination also occurring at a number of additional sites, including the kidney and other tissues. Approximately 80% of the daily dose of T4 is deiodinated to yield equal amounts of T3 and reverse T3 (rT3). T3 and rT3 are further deiodinated to diiodothyronine. Thyroid hormones are also metabolized via conjugation with glucuronides and sulfates and excreted directly into the bile and gut where they undergo enterohepatic recirculation.

Excretion

Thyroid hormones are primarily eliminated by the kidneys. A portion of the conjugated hormone reaches the colon unchanged and is eliminated in the feces. Approximately 20% of T4 is eliminated in the stool. Urinary excretion of T4 decreases with age.

Table 10. Pharmacokinetic Parameters of Thyroid Hormones in Euthyroid Patients
Hormone | Ratio in Thyroglobulin | Biologic Potency | t1/2 (days) | Protein Binding (%)*
Levothyroxine (T4) | 10 - 20 | 1 | 6-7** | 99.96
Liothyronine (T3) | 1 | 4 | ≤ 2 | 99.5
* Includes TBG, TBPA, and TBA
** 3 to 4 days in hyperthyroidism, 9 to 10 days in hypothyroidism

13 NONCLINICAL TOXICOLOGY

13.1 Carcinogenesis, Mutagenesis, Impairment of Fertility

Long-term carcinogenicity studies in animals to evaluate the carcinogenic potential of levothyroxine have not been performed. Studies to evaluate mutagenic potential and animal fertility have not been performed.

16 HOW SUPPLIED/STORAGE AND HANDLING

Product: 50090-7862

NDC: 50090-7862-0 90 TABLET in a BOTTLE

17 PATIENT COUNSELING INFORMATION

Inform the patient of the following information to aid in the safe and effective use of Levothyroxine Sodium Tablets:

Dosing and Administration

- Instruct patients to take Levothyroxine Sodium Tablets only as directed by their healthcare provider.
- Instruct patients to take Levothyroxine Sodium Tablets as a single dose, preferably on an empty stomach, one-half to one hour before breakfast.
- Inform patients that agents such as iron and calcium supplements and antacids can decrease the absorption of levothyroxine. Instruct patients not to take Levothyroxine Sodium Tablets within 4 hours of these agents.
- Instruct patients to notify their healthcare provider if they are pregnant or breastfeeding or are thinking of becoming pregnant while taking Levothyroxine Sodium Tablets.

Important Information

- Inform patients that it may take several weeks before they notice an improvement in symptoms.
- Inform patients that the levothyroxine in Levothyroxine Sodium Tablets is intended to replace a hormone that is normally produced by the thyroid gland. Generally, replacement therapy is to be taken for life.
- Inform patients that Levothyroxine Sodium Tablets should not be used as a primary or adjunctive therapy in a weight control program.
- Instruct patients to notify their healthcare provider if they are taking any other medications, including prescription and over-the-counter preparations.
- Instruct patients to notify their physician of any other medical conditions they may have, particularly heart disease, diabetes, clotting disorders, and adrenal or pituitary gland problems, as the dose of medications used to control these other conditions may need to be adjusted while they are taking Levothyroxine Sodium Tablets. If they have diabetes, instruct patients to monitor their blood and/or urinary glucose levels as directed by their physician and immediately report any changes to their physician. If patients are taking anticoagulants, their clotting status should be checked frequently.
- Instruct patients to notify their physician or dentist that they are taking Levothyroxine Sodium Tablets prior to any surgery.

Adverse Reactions

- Instruct patients to notify their healthcare provider if they experience any of the following symptoms: rapid or irregular heartbeat, chest pain, shortness of breath, leg cramps, headache, nervousness, irritability, sleeplessness, tremors, change in appetite, weight gain or loss, vomiting, diarrhea, excessive sweating, heat intolerance, fever, changes in menstrual periods, hives or skin rash, or any other unusual medical event.
- Inform patients that partial hair loss may occur rarely during the first few months of Levothyroxine Sodium Tablets therapy, but this is usually temporary.

Manufactured by:
LLOYD, Inc.
Shenandoah, IA 51601 USA

Distributed by:
Alvogen, Inc.
Pine Brook, NJ 07058 USA

PI640-01